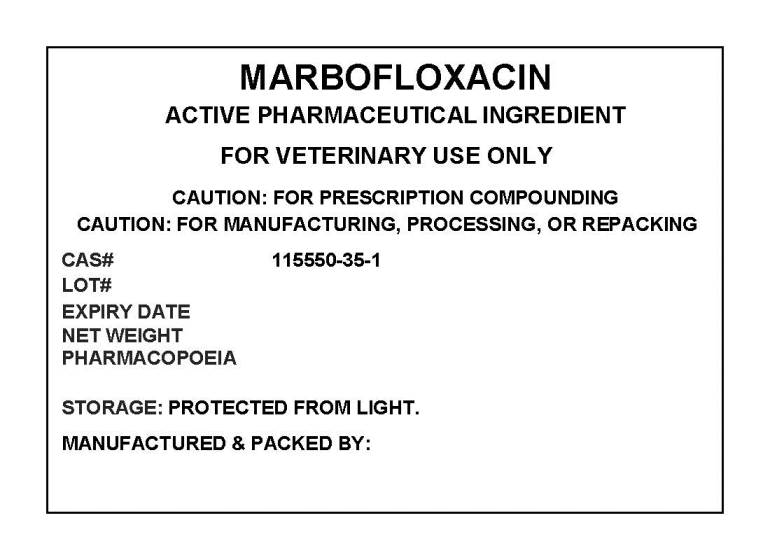 DRUG LABEL: MARBOFLOXACIN
NDC: 72969-042 | Form: POWDER
Manufacturer: PROFESSIONAL GROUP OF PHARMACISTS NEW YORK LLC
Category: other | Type: BULK INGREDIENT
Date: 20210310

ACTIVE INGREDIENTS: MARBOFLOXACIN 1 g/1 g

MARBOFLOXACIN

PACKAGE LABEL

marbofloxacinlabel.jpg